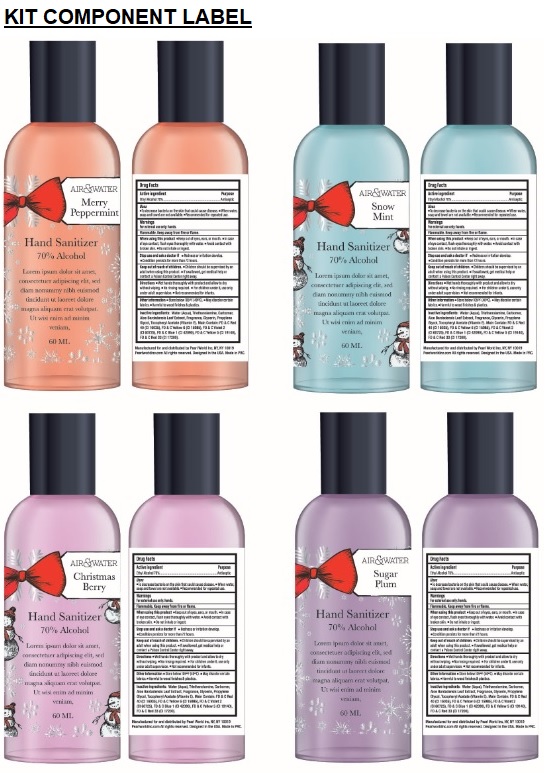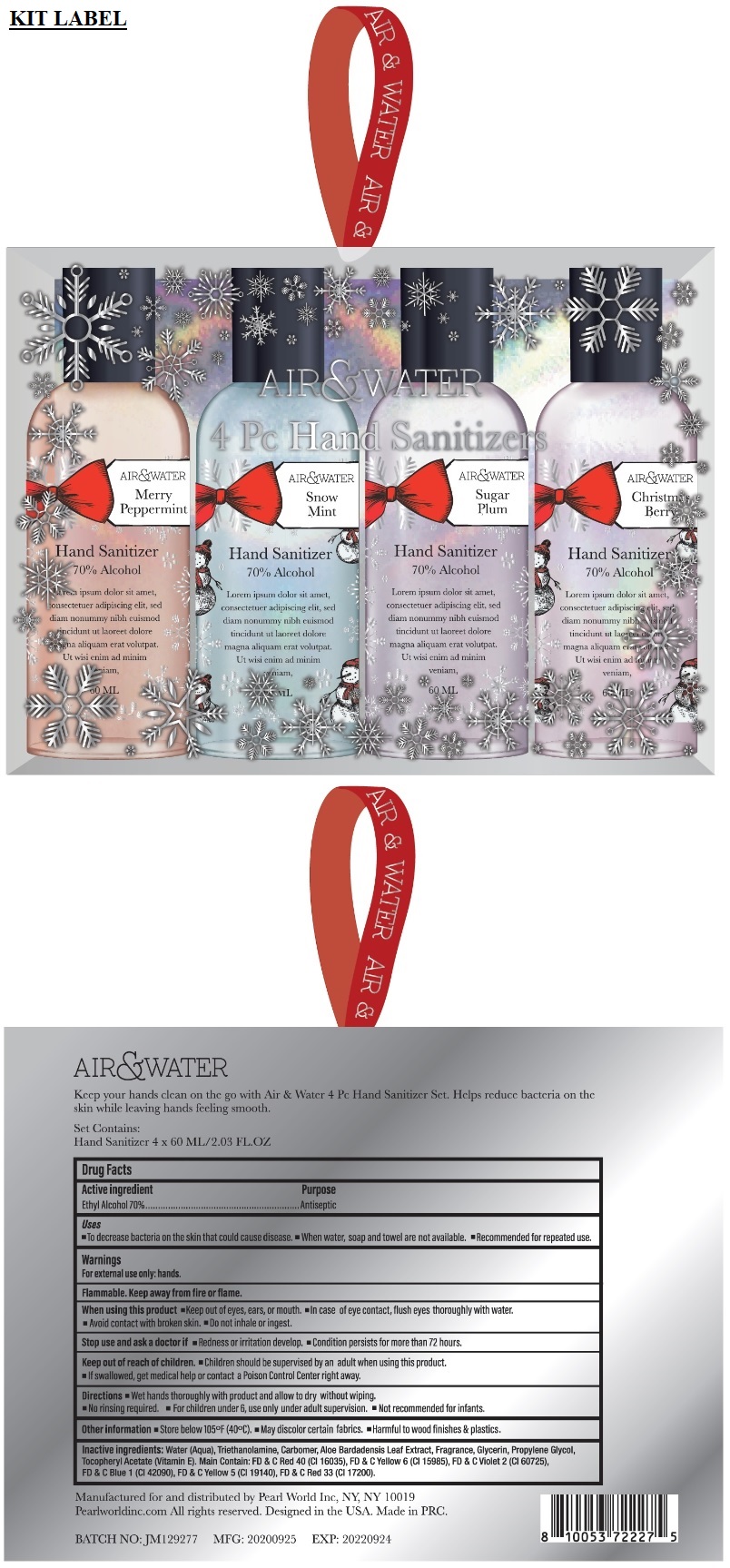 DRUG LABEL: Air and Water Hand Sanitizer Kit
NDC: 69933-404 | Form: KIT | Route: TOPICAL
Manufacturer: Pearl World Inc.
Category: otc | Type: HUMAN OTC DRUG LABEL
Date: 20200921

ACTIVE INGREDIENTS: ALCOHOL 70 mL/100 mL; ALCOHOL 70 mL/100 mL; ALCOHOL 70 mL/100 mL; ALCOHOL 70 mL/100 mL
INACTIVE INGREDIENTS: WATER; TROLAMINE; CARBOMER HOMOPOLYMER, UNSPECIFIED TYPE; ALOE VERA LEAF; GLYCERIN; PROPYLENE GLYCOL; .ALPHA.-TOCOPHEROL ACETATE; FD&C RED NO. 40; FD&C YELLOW NO. 6; D&C VIOLET NO. 2; FD&C BLUE NO. 1; FD&C YELLOW NO. 5; D&C RED NO. 33; WATER; TROLAMINE; CARBOMER HOMOPOLYMER, UNSPECIFIED TYPE; ALOE VERA LEAF; GLYCERIN; PROPYLENE GLYCOL; .ALPHA.-TOCOPHEROL ACETATE; FD&C RED NO. 40; FD&C YELLOW NO. 6; D&C VIOLET NO. 2; FD&C BLUE NO. 1; FD&C YELLOW NO. 5; D&C RED NO. 33; WATER; TROLAMINE; CARBOMER HOMOPOLYMER, UNSPECIFIED TYPE; ALOE VERA LEAF; GLYCERIN; PROPYLENE GLYCOL; .ALPHA.-TOCOPHEROL ACETATE; FD&C RED NO. 40; FD&C YELLOW NO. 6; D&C VIOLET NO. 2; FD&C BLUE NO. 1; FD&C YELLOW NO. 5; D&C RED NO. 33; WATER; TROLAMINE; CARBOMER HOMOPOLYMER, UNSPECIFIED TYPE; ALOE VERA LEAF; GLYCERIN; PROPYLENE GLYCOL; .ALPHA.-TOCOPHEROL ACETATE; FD&C RED NO. 40; FD&C YELLOW NO. 6; D&C VIOLET NO. 2; FD&C BLUE NO. 1; FD&C YELLOW NO. 5; D&C RED NO. 33

AIR&WATER Hand Sanitizer Kit

Active ingredient

Ethyl Alcohol 70%

Purpose

Antiseptic

Uses

• To decrease bacteria on the skin that could cause disease. • When water, soap and towel are not available. • Recommended for repeated use.

Warnings

For external use only: hands.

Flammable. Keep away from fire or flame.

When using this product • Keep out of eyes, ears, or mouth. • In case of eye contact, flush eyes thoroughly with water. • Avoid contact with broken skin. • Do not inhale or ingest.

Stop use and ask a doctor if • Redness or irritation develop • Condition persists for more than 72 hours.

Keep out of reach of children. • Children should be supervised by an adult when using this product. • If swallowed, get medical help or contact a Poison Control Center right away.

DOSAGE AND ADMINISTRATION

Directions • Wet hands thoroughly with product and allow to dry without wiping. • No rinsing required. • For children under 6, use only under adult supervision. • Not recommended for infants.

Other information • Store below 105°F (40°C). • May discolor certain fabrics. • Harmful to wood finishes & plastics.

INACTIVE INGREDIENT

Inactive ingredients: Water (Aqua), Triethanolamine, Carbomer, Aloe Barbadensis Leaf Extract, Fragrance, Glycerin, Propylene Glycol, Tocopheryl Acetate (Vitamin E). Main Contain: FD & C Red 40 (CI 16035), FD & C Yellow 6 (CI 15985), FD & C Violet 2 (CI 60725), FD & C Blue 1 (CI 42090), FD & C Yellow 5 (CI 19140), FD & C Red 33(CI 17200).

70% Alcohol

Manufactured for and distributed by Pearl world Inc, NY, NY 10019
Pearlworldinc.com All rights reserved. Designed in the USA. Made in PRC.

Active ingredient

Ethyl Alcohol 70%

Purpose

Antiseptic

Uses

• To decrease bacteria on the skin that could cause disease. • When water, soap and towel are not available. • Recommended for repeated use.

Warnings

For external use only: hands.

Flammable. Keep away from fire or flame.

When using this product • Keep out of eyes, ears, or mouth. • In case if eye contact, flush eyes thoroughly with water. • Avoid contact with broken skin. • Do not inhale or ingest.

Stop use and ask a doctor if • Redness or irritation develop • Condition persists for more than 72 hours.

Keep out of reach of children. • Children should be supervised by an adult when using this product. • if swallowed, get medical help or contact a Poison Control Center right away.

DOSAGE AND ADMINISTRATION

Directions • Wet hands thoroughly with product and allow to dry without wiping. • No rinsing required. • For children under 6, use only under adult supervision. • Not recommended for infants.

Other information • Store below 105°F (40°C). • May discolor certain fabrics. • Harmful to wood finishes & plastics.

INACTIVE INGREDIENT

Inactive ingredients: Water (Aqua), Triethanolamine, Carbomer, Aloe Barbadensis Leaf Extract, Fragrance, Glycerin, Propylene Glycol, Tocopheryl Acetate (Vitamin E). Main Contain: FD & C Red 40 (CI 16035), FD & C Yellow 6 (CI 15985), FD & C Violet 2 (CI 60725), FD & C Blue 1 (CI 42090), FD & C Yellow 5 (CI 19140), FD & C Red 33 (CI 17200).

70% Alcohol

Manufactured for and distributed by Pearl World Inc, NY, NY 10019 Pearlworldinc.com

All rights reserved. Designed in the USA. Made in PRC.

Active ingredient

Ethyl Alcohol 70%

Purpose

Antiseptic

Uses

• To decrease bacteria on the skin that could cause disease. • When water, soap and towel are not available. • Recommended for repeated use.

Warnings

For external use only: hands.

Flammable. Keep away from fire or flame.

When using this product • Keep out of eyes, ears, or mouth. • In case of eye contact, flush eyes thoroughly with water. • Avoid contact with broken skin. • Do not inhale or ingest.

Stop use and ask a doctor if • Redness or irritation develop. • Condition persists for more than 72 hours.

Keep out of reach of children. • Children should be supervised by an adult when using this product. • If swallowed, get medical help or contact a Poison Control Center right away.

DOSAGE AND ADMINISTRATION

Directions • Wet hands thoroughly with product and allow to dry without wiping. • No rinsing required. • For children under 6, use only under adult supervision. • Not recommended for infants.

Other information • Store below 105°F (40°C) • May discolor certain fabrics. • Harmful to wood finishes & plastics.

INACTIVE INGREDIENT

Inactive ingredients: Water (Aqua), Triethanolamine, Carbomer, Aloe Barbadensis Leaf Extract, Fragrance, Glycerin, Propylene Glycol, Tocopheryl Acetate (Vitamin E). Main Contain: FD & C Red 40 (CI 16035), FD & C Yellow 6 (CI 15985), FD & C Violet 2 (CI 60725), FD & C Blue 1 (CI 42090), FD & C Yellow 5 (CI 19140), FD & C Red 33(CI 17200).

Active ingredient

Ethyl Alcohol 70%

Purpose

Antiseptic

Uses

• To decrease bacteria on the skin that could cause disease. • When water, soap and towel are not available. • Recommended for repeated use.

Warnings

For external use only: hands.

Flammable. Keep away from fire or flame.

When using this product • Keep out of eyes, ears, or mouth. • In case of eye contact, flush eyes thoroughly with water. • Avoid contact with broken skin. • Do not inhale or ingest.

Stop use and ask a doctor if • Redness or irritation develop. • Condition persists for more than 72 hours.

Keep out of reach of children. • Children should be supervised by an adult when using this product. • If swallowed, get medical help or contact a Poison Control Center right away.

DOSAGE AND ADMINISTRATION

Directions • Wet hands thoroughly with product and allow to dry without wiping. • No rinsing required. • For children under 6, use only under adult supervision. • Not recommended for infants.

Other information • Store below 105°F (40°C). • May discolor certain fabrics. • Harmful to wood finishes & plastics.

INACTIVE INGREDIENT

Inactive ingredients: Water (Aqua), Triethanolamine, Carbomer, Aloe Barbadensis Leaf Extract, Fragrance, Glycerin, Propylene Glycol, Tocopheryl Acetate (Vitamin E). Main Contain: FD & C Red 40 (CI 16035), FD & C Yellow 6 (CI 15985), FD & C Violet 2 (CI 60725), FD & C Blue 1 (CI 42090), FD & C Yellow 5 (CI 19140), FD & C Red 33(CI 17200).

70% Alcohol

Manufactured for and distributed by Pearl world Inc, NY, NY 10019

Pearlworldinc.com All rights reserved. Designed in the USA. Made in PRC.